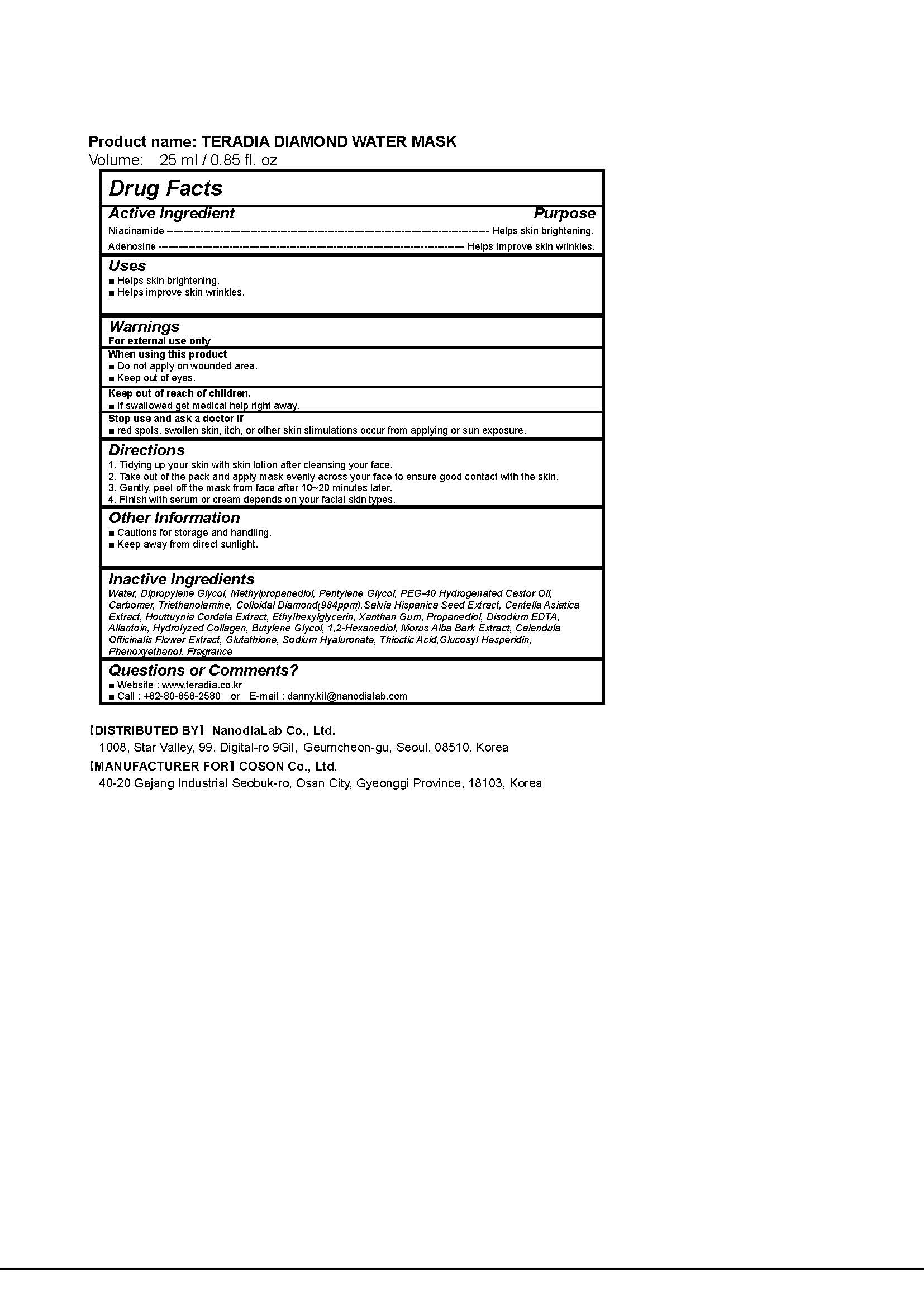 DRUG LABEL: TERADIA DIAMOND WATER MASK
NDC: 71483-0003 | Form: LIQUID
Manufacturer: NanoDia Lab Co Ltd
Category: otc | Type: HUMAN OTC DRUG LABEL
Date: 20181218

ACTIVE INGREDIENTS: ADENOSINE 0.04 g/100 mL; NIACINAMIDE 2 g/100 mL
INACTIVE INGREDIENTS: WATER

Drug Facts

ACTIVE INGREDIENT

Niacinamide, Adenosine

INACTIVE INGREDIENT

Water, etc

PURPOSE

Anti-Wrinkle, Whitening

keep out of reach of the children

INDICATIONS AND USAGE

1. Tidying up your skin with skin lotion after cleansing your face.
2. Take out of the pack and apply mask evenly across your face to ensure good contact with the skin.
3. Gently, peel off the mask from face after 10~20 minutes later.
4. Finish with serum or cream depends on your facial skin types.

WARNINGS

1. Do not use in the following cases(Eczema and scalp wounds)
2.Side Effects
1)Due to the use of this druf if rash, irritation, itching and symptopms of hypersnesitivity occur dicontinue use and consult your phamacisr or doctor
3.General Precautions
1)If in contact with the eyes, wash out thoroughty with water If the symptoms are servere, seek medical advice immediately
2)This product is for exeternal use only. Do not use for internal use
4.Storage and handling precautions
1)If possible, avoid direct sunlight and store in cool and area of low humidity
2)In order to maintain the quality of the product and avoid misuse
3)Avoid placing the product near fire and store out in reach of children

DOSAGE AND ADMINISTRATION

for external use only